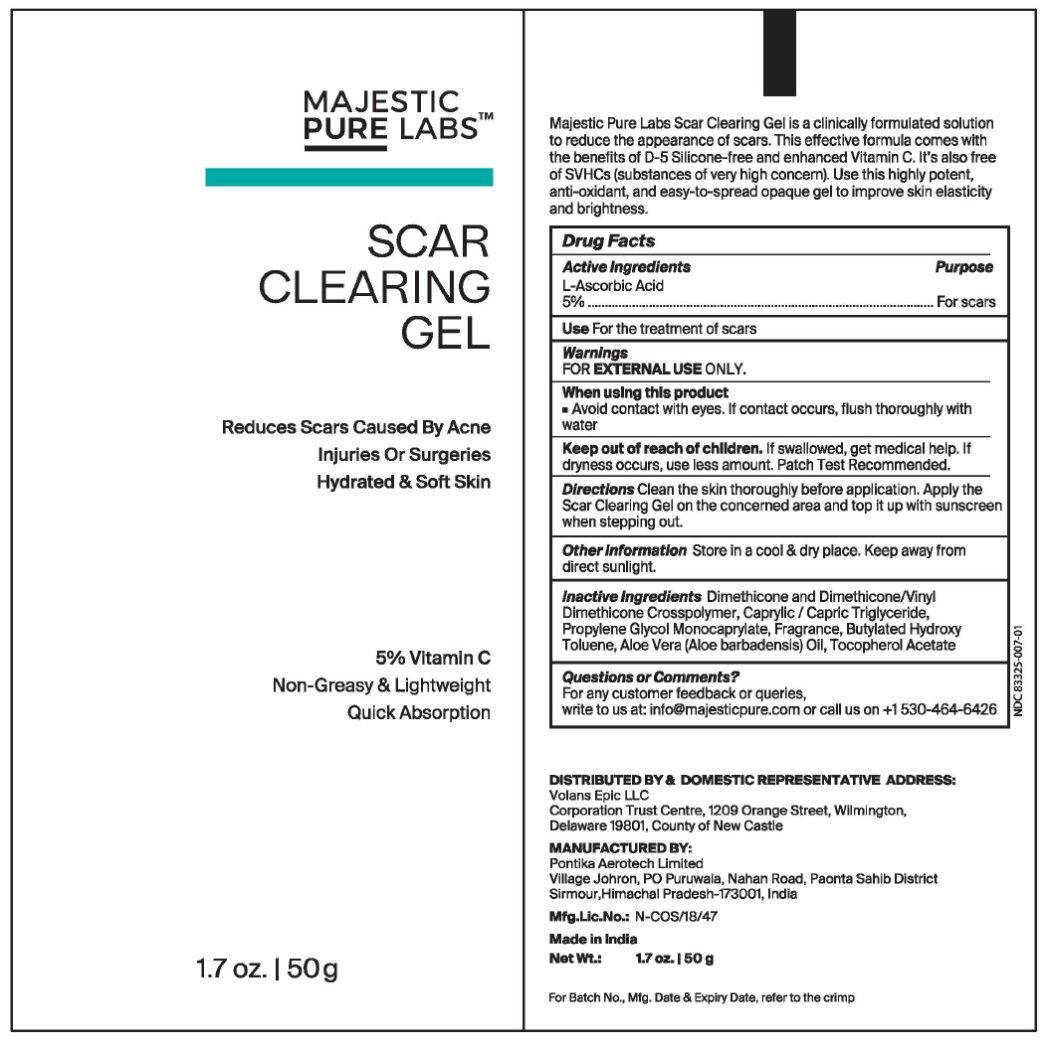 DRUG LABEL: scar clearing
NDC: 83325-007 | Form: LOTION
Manufacturer: Volans Epic LLC
Category: otc | Type: HUMAN OTC DRUG LABEL
Date: 20240207

ACTIVE INGREDIENTS: ASCORBIC ACID 5 g/50 g
INACTIVE INGREDIENTS: DIMETHICONE; TRICAPRIN; PROPYLENE GLYCOL MONOCAPRYLATE; FRAGRANCE 13576; BUTYLATED HYDROXYANISOLE; ALOE VERA LEAF; .ALPHA.-TOCOPHEROL ACETATE

SCAR
CLEARING
GEL
Reduces Scars Caused By Acne
Injuries Or Surgeries
Hydrated & Soft Skin
5% Vitamin C
Non-Greasy & Lightweight
Quick Absorption
1.7 oz. 50g

Active Ingredients Purpose

L-Ascorbic Acid 5%-----------------------------------------For scars

Use

For the treatment of scars

Warnings

FOR EXTERNAL USEONLY.

When using this product

■ Avoid contact with eyes. If contact occurs, flush thoroughly with water

Keep out of reach of children.If swallowed, get medical help. If dryness occurs, use less amount. Patch Test Recommended.

Directions

Clean the skin thoroughly before application. Apply the Scar Clearing Gel on the concerned area and top it up with sunscreen when stepping out.

Other Information

Store in a cool & dry place. Keep away from direct sunlight.

Inactive Ingredients

Dimethicone and Dimethicone/Vinyl Dimethicone Crosspolymer, Caprylic/Capric Triglyceride, Propylene Glycol Monocaprylate, Fragrance, Butylated Hydroxy Toluene, Aloe Vera (Aloe barbadensis) Oil, Tocopherol Acetate.

Questions or Comments?

For any customer feedback or queries,
write to us at: info@majesticpure.com or call us on +1 530-464-6426

DISTRIBUTED BY & DOMESTIC REPRESENTATIVE ADDRESS:
Volans Epic LLC
Corporation Trust Centre, 1209 Orange Street, Wilmington,
Delaware 19801, County of New Castle

MANUFACTURED BY:
Pontika Aerotech Limited
Village Johron, PO Puruwala, Nahan Road, Paonta Sahib District
Sirmour, Himachal Pradesh-173001, India

Mfg.Lic.No.:N-COS/18/47

Mada in India

PACKAGE LABEL. PRINCIPAL DISPLAY PANEL

SCAR CLEARING GEL (1.7 oz & 50g)- NDC-83325-007-01- Bottle Label